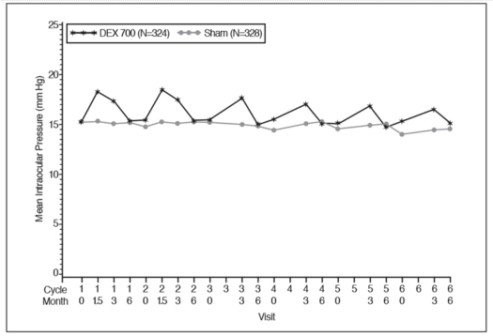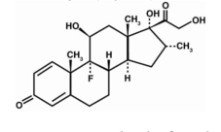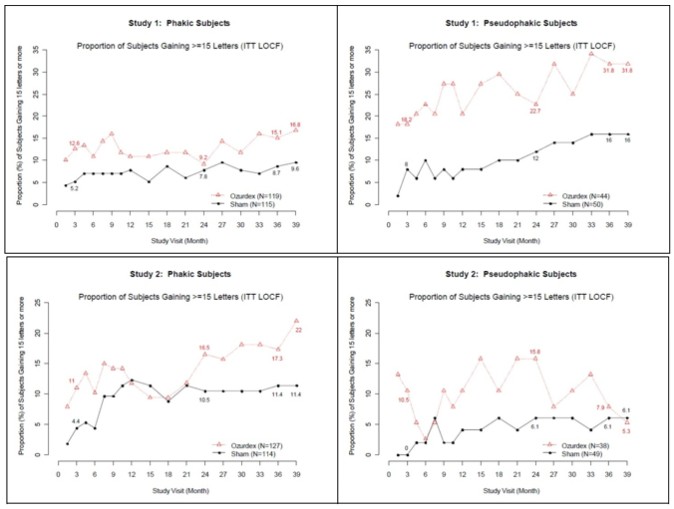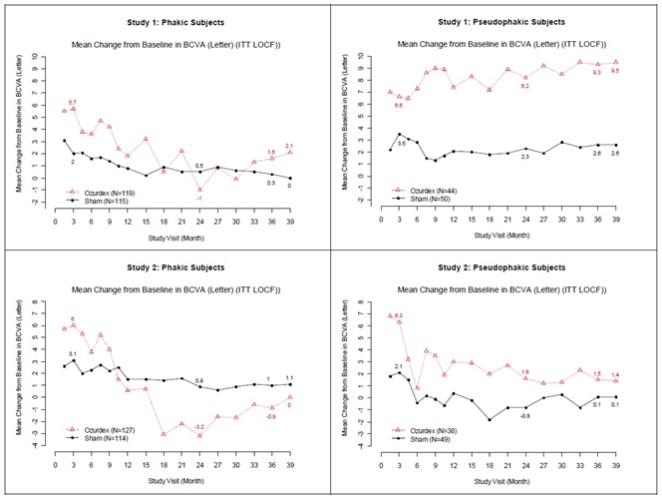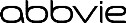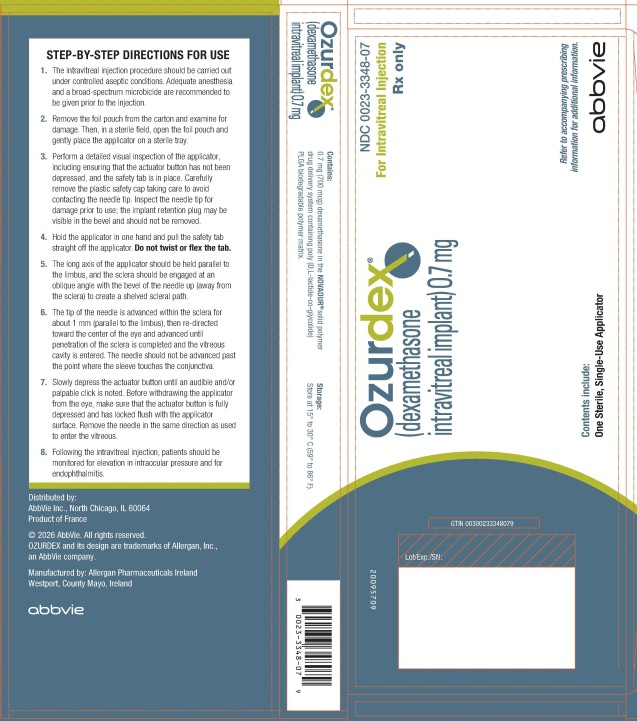 DRUG LABEL: OZURDEX
NDC: 0023-3348 | Form: IMPLANT
Manufacturer: Allergan, Inc.
Category: prescription | Type: HUMAN PRESCRIPTION DRUG LABEL
Date: 20260227

ACTIVE INGREDIENTS: DEXAMETHASONE 0.7 mg/1 1
INACTIVE INGREDIENTS: DL-LACTIDE AND GLYCOLIDE (50:50) COPOLYMER 12000 ETHYL ESTER; DL-LACTIDE AND GLYCOLIDE (50:50) COPOLYMER 12000 ACID

HIGHLIGHTS OF PRESCRIBING INFORMATION

These highlights do not include all the information needed to use OZURDEX safely and effectively. See full prescribing information for OZURDEX.
OZURDEX® (dexamethasone intravitreal implant),
for intravitreal injection
Initial U.S. Approval: 1958

RECENT MAJOR CHANGES

Dosage and Administration, Administration (2.2) 2/2026

1 INDICATIONS AND USAGE

OZURDEX is a corticosteroid indicated for:

- The treatment of macular edema following branch retinal vein occlusion (BRVO) or central retinal vein occlusion (CRVO) (1.1)
- The treatment of non-infectious uveitis affecting the posterior segment of the eye (1.2)
- The treatment of diabetic macular edema (1.3)

2 DOSAGE AND ADMINISTRATION

For ophthalmic intravitreal injection. (2.1)

- The intravitreal injection procedure should be carried out under controlled aseptic conditions. (2.2)
- Following the intravitreal injection, patients should be monitored for elevation in intraocular pressure and for endophthalmitis. (2.2)

3 DOSAGE FORMS AND STRENGTHS

Intravitreal implant containing dexamethasone 0.7 mg in the NOVADUR® solid polymer drug delivery system. (3)

4 CONTRAINDICATIONS

- Ocular or periocular infections (4.1)
- Glaucoma (4.2)
- Torn or ruptured posterior lens capsule (4.3)
- Hypersensitivity (4.4)

5 WARNINGS AND PRECAUTIONS

- Intravitreal injections have been associated with endophthalmitis, eye inflammation, increased intraocular pressure, and retinal detachments. Patients should be monitored following the injection. (5.1)
- Use of corticosteroids may produce posterior subcapsular cataracts, increased intraocular pressure, glaucoma, and may enhance the establishment of secondary ocular infections due to bacteria, fungi, or viruses. (5.2)

6 ADVERSE REACTIONS

In controlled studies, the most common adverse reactions reported by 20–70% of patients were cataract, increased intraocular pressure and conjunctival hemorrhage. (6.1)

To report SUSPECTED ADVERSE REACTIONS, contact AbbVie at 1-800-633-9110 or FDA at 1-800-FDA-1088 or www.fda.gov/medwatch.

FULL PRESCRIBING INFORMATION

1 INDICATIONS AND USAGE

1.1 Retinal Vein Occlusion

OZURDEX® (dexamethasone intravitreal implant) is indicated for the treatment of macular edema following branch retinal vein occlusion (BRVO) or central retinal vein occlusion (CRVO).

1.2 Posterior Segment Uveitis

OZURDEX is indicated for the treatment of non-infectious uveitis affecting the posterior segment of the eye.

1.3 Diabetic Macular Edema

OZURDEX is indicated for the treatment of diabetic macular edema.

2 DOSAGE AND ADMINISTRATION

2.1 General Dosing Information

For ophthalmic intravitreal injection.

2.2 Administration

The intravitreal injection procedure should be carried out under controlled aseptic conditions which include the use of sterile gloves, a sterile drape, and a sterile eyelid speculum (or equivalent). Adequate anesthesia and a broad-spectrum microbicide applied to the periocular skin, eyelid and ocular surface are recommended to be given prior to the injection.

Remove the foil pouch from the carton and examine for damage. Then, open the foil pouch over a sterile field and gently drop the applicator on a sterile tray. Perform a detailed visual inspection of the applicator, including ensuring that the actuator button has not been depressed, and the safety tab is in place. Carefully remove the plastic safety cap taking care to avoid contacting the needle tip. Inspect the needle tip for damage prior to use; the implant retention plug may be visible in the bevel and should not be removed. Hold the applicator in one hand and pull the safety tab straight off the applicator. Do not twist or flex the tab. The long axis of the applicator should be held parallel to the limbus, and the sclera should be engaged at an oblique angle with the bevel of the needle up (away from the sclera) to create a shelved scleral path. The tip of the needle is advanced within the sclera for about 1 mm (parallel to the limbus), then re-directed toward the center of the eye and advanced until penetration of the sclera is completed and the vitreous cavity is entered. The needle should not be advanced past the point where the sleeve touches the conjunctiva.

Slowly depress the actuator button until an audible and/or palpable click is noted. Before withdrawing the applicator from the eye, make sure that the actuator button is fully depressed and has locked flush with the applicator surface. Remove the needle in the same direction as used to enter the vitreous.

Following the intravitreal injection, patients should be monitored for elevation in intraocular pressure and for endophthalmitis. Monitoring may consist of a check for perfusion of the optic nerve head immediately after the injection, tonometry within 30 minutes following the injection, and biomicroscopy between two and seven days following the injection. Patients should be instructed to report any symptoms suggestive of endophthalmitis without delay.

Each applicator can only be used for the treatment of a single eye. If the contralateral eye requires treatment, a new applicator must be used, and the sterile field, syringe, gloves, drapes, and eyelid speculum should be changed before OZURDEX is administered to the other eye.

3 DOSAGE FORMS AND STRENGTHS

Intravitreal implant containing dexamethasone 0.7 mg in the NOVADUR® solid polymer drug delivery system.

4 CONTRAINDICATIONS

4.1 Ocular or Periocular Infections

OZURDEX (dexamethasone intravitreal implant) is contraindicated in patients with active or suspected ocular or periocular infections including most viral diseases of the cornea and conjunctiva, including active epithelial herpes simplex keratitis (dendritic keratitis), vaccinia, varicella, mycobacterial infections, and fungal diseases.

4.2 Glaucoma

OZURDEX is contraindicated in patients with glaucoma, who have cup to disc ratios of greater than 0.8.

4.3 Torn or Ruptured Posterior Lens Capsule

OZURDEX is contraindicated in patients whose posterior lens capsule is torn or ruptured because of the risk of migration into the anterior chamber. Laser posterior capsulotomy in pseudophakic patients is not a contraindication for OZURDEX use.

4.4 Hypersensitivity

OZURDEX is contraindicated in patients with known hypersensitivity to any components of this product [see Adverse Reactions (6)].

5 WARNINGS AND PRECAUTIONS

5.1 Intravitreal Injection-related Effects

Intravitreal injections, including those with OZURDEX, have been associated with endophthalmitis, eye inflammation, increased intraocular pressure, and retinal detachments. Patients should be monitored regularly following the injection [see Patient Counseling Information (17)].

5.2 Steroid-related Effects

Use of corticosteroids including OZURDEX may produce posterior subcapsular cataracts, increased intraocular pressure, and glaucoma. Use of corticosteroids may enhance the establishment of secondary ocular infections due to bacteria, fungi, or viruses [see Adverse Reactions (6.1)].

Corticosteroids are not recommended to be used in patients with a history of ocular herpes simplex because of the potential for reactivation of the viral infection.

6 ADVERSE REACTIONS

6.1 Clinical Trials Experience

Because clinical trials are conducted under widely varying conditions, adverse reaction rates observed in the clinical studies of a drug cannot be directly compared to rates in the clinical studies of another drug and may not reflect the rates observed in practice.

Adverse reactions associated with ophthalmic steroids including OZURDEX include elevated intraocular pressure, which may be associated with optic nerve damage, visual acuity and field defects, posterior subcapsular cataract formation, secondary ocular infection from pathogens including herpes simplex, and perforation of the globe where there is thinning of the cornea or sclera.

Retinal Vein Occlusion and Posterior Segment Uveitis

The following information is based on the combined clinical trial results from 3 initial, randomized, 6-month, sham-controlled studies (2 for retinal vein occlusion and 1 for posterior segment uveitis):

Table 1: Adverse Reactions Reported by Greater than 2% of Patients
MedDRA Term | OZURDEX N=497 (%) | Sham N=498 (%)
Intraocular pressure increased | 125 (25%) | 10 (2%)
Conjunctival hemorrhage | 108 (22%) | 79 (16%)
Eye pain | 40 (8%) | 26 (5%)
Conjunctival hyperemia | 33 (7%) | 27 (5%)
Ocular hypertension | 23 (5%) | 3 (1%)
Cataract | 24 (5%) | 10 (2%)
Vitreous detachment | 12 (2%) | 8 (2%)
Headache | 19 (4%) | 12 (2%)

Increased IOP with OZURDEX peaked at approximately week 8. During the initial treatment period, 1% (3/421) of the patients who received OZURDEX required surgical procedures for management of elevated IOP.

Following a second injection of OZURDEX in cases where a second injection was indicated, the overall incidence of cataracts was higher after 1 year.

In a 2 year observational study, among patients who received >2 injections, the most frequent adverse reaction was cataract 54% (n= 96 out of 178 phakic eyes at baseline). Other frequent adverse reactions from the 283 treated eyes, regardless of lens status at baseline, were increased IOP 24% (n = 68) and vitreous hemorrhage 6.0% (n = 17).

Diabetic Macular Edema

The following information is based on the combined clinical trial results from 2 randomized, 3-year, sham-controlled studies in patients with diabetic macular edema. Discontinuation rates due to the adverse reactions listed in Table 2 were 3% in the OZURDEX group and 1% in the Sham group. The most common ocular (study eye) and non-ocular adverse reactions are shown in Tables 2 and 3:

Table 2: Ocular Adverse Reactions Reported by ≥ 1% of Patients and Non-ocular Adverse Reactions Reported by ≥ 5% of Patients
MedDRA Term | OZURDEX N=324 (%) | Sham N=328 (%)
Ocular
Cataract^1 | 166/243^2 (68%) | 49/230 (21%)
Conjunctival hemorrhage | 73 (23%) | 44 (13%)
Visual acuity reduced | 28 (9%) | 13 (4%)
Conjunctivitis | 19 (6%) | 8 (2%)
Vitreous floaters | 16 (5%) | 6 (2%)
Conjunctival edema | 15 (5%) | 4 (1%)
Dry eye | 15 (5%) | 7 (2%)
Vitreous detachment | 14 (4%) | 8 (2%)
Vitreous opacities | 11 (3%) | 3 (1%)
Retinal aneurysm | 10 (3%) | 5 (2%)
Foreign body sensation | 7 (2%) | 4 (1%)
Corneal erosion | 7 (2%) | 3 (1%)
Keratitis | 6 (2%) | 3 (1%)
Anterior Chamber Inflammation | 6 (2%) | 0 (0%)
Retinal tear | 5 (2%) | 2 (1%)
Eyelid ptosis | 5 (2%) | 2 (1%)
Non-ocular
Hypertension | 41 (13%) | 21 (6%)
Bronchitis | 15 (5%) | 8 (2%)

^1 Includes cataract, cataract nuclear, cataract subcapsular, lenticular opacities in patients who were phakic at baseline. Among these patients, 61% of OZURDEX subjects vs. 8% of sham-controlled subjects underwent cataract surgery.

^2 243 of the 324 OZURDEX subjects were phakic at baseline; 230 of 328 sham-controlled subjects were phakic at baseline.

Increased Intraocular Pressure

Table 3: Summary of Elevated Intraocular Pressure (IOP) Related Adverse Reactions
IOP | Treatment: N (%)
 | OZURDEX N=324 | Sham N=328
IOP elevation ≥10 mm Hg from Baseline at any visit | 91 (28%) | 13 (4%)
≥30 mm Hg IOP at any visit | 50 (15%) | 5 (2%)
Any IOP lowering medication | 136 (42%) | 32 (10%)
Any surgical intervention for elevated IOP * | 4 (1.2%) | 1 (0.3%)

* OZURDEX: 1 surgical trabeculectomy for steroid-induced IOP increase, 1 surgical trabeculectomy for iris neovascularization,
1 laser iridotomy, 1 surgical iridectomy
Sham: 1 laser iridotomy

The increase in mean IOP was seen with each treatment cycle, and the mean IOP generally returned to baseline between treatment cycles (at the end of the 6 month period) shown below:

Figure 1: Mean IOP during the study

Cataracts and Cataract Surgery

At baseline, 243 of the 324 OZURDEX subjects were phakic; 230 of 328 sham-controlled subjects were phakic. The incidence of cataract development in patients who had a phakic study eye was higher in the OZURDEX group (68%) compared with Sham (21%). The median time of cataract being reported as an adverse event was approximately 15 months in the OZURDEX group and 12 months in the Sham group. Among these patients, 61% of OZURDEX subjects vs. 8% of sham-controlled subjects underwent cataract surgery, generally between Month 18 and Month 39 (Median Month 21 for OZURDEX group and 20 for Sham) of the studies.

6.2 Postmarketing Experience

The following reactions have been identified during post-approval use of OZURDEX in clinical practice. Because they are reported voluntarily from a population of unknown size, estimates of frequency cannot be made. The reactions, which have been chosen for inclusion due to either their seriousness, frequency of reporting, possible causal connection to OZURDEX, or a combination of these factors, include: complication of device insertion resulting in ocular tissue injury including sclera, subconjunctiva, lens and retina (implant misplacement), device dislocation with or without corneal edema, endophthalmitis, hypotony of the eye (associated with vitreous leakage due to injection), and retinal detachment.

8 USE IN SPECIFIC POPULATIONS

8.1 Pregnancy

Risk Summary

There are no adequate and well-controlled studies with OZURDEX in pregnant women. Topical ocular administration of dexamethasone in mice and rabbits during the period of organogenesis produced cleft palate and embryofetal death in mice, and malformations of the abdominal wall/intestines and kidneys in rabbits at doses 5 and 4 times higher than the recommended human ophthalmic dose (RHOD) of OZURDEX (0.7 milligrams dexamethasone), respectively.

In the US general population, the estimated background risk of major birth defects and miscarriage in clinically recognized pregnancies is 2 to 4% and 15 to 20%, respectively.

Data

Animal Data

Topical ocular administration of 0.15% dexamethasone (0.75 mg/kg/day) on gestational days 10 to 13 produced embryofetal lethality and a high incidence of cleft palate in mice. A dose of 0.75 mg/kg/day in the mouse is approximately 5 times an OZURDEX injection in humans (0.7 mg dexamethasone) on a mg/m^2 basis. In rabbits, topical ocular administration of 0.1% dexamethasone throughout organogenesis (0.20 mg/kg/day, on gestational day 6 followed by 0.13 mg/kg/day on gestational days 7-18) produced intestinal anomalies, intestinal aplasia, gastroschisis and hypoplastic kidneys. A dose of 0.13 mg/kg/day in the rabbit is approximately 4 times an OZURDEX injection in humans (0.7 mg dexamethasone) on a mg/m^2 basis. A no-observed-adverse-effect-level (NOAEL) was not identified in the mouse or rabbits studies.

8.2 Lactation

Risk Summary

Systemically administered corticosteroids are present in human milk and can suppress growth and interfere with endogenous corticosteroid production or cause other unwanted effects. There is no information regarding the presence of dexamethasone in human milk, the effects on the breastfed infants, or the effects on milk production to inform risk of OZURDEX to an infant during lactation. The developmental and health benefits of breastfeeding should be considered, along with the mother’s clinical need for OZURDEX and any potential adverse effects on the breastfed child from OZURDEX.

8.4 Pediatric Use

Safety and effectiveness of OZURDEX in pediatric patients have not been established.

8.5 Geriatric Use

No overall differences in safety or effectiveness have been observed between elderly and younger patients.

11 DESCRIPTION

OZURDEX is a sterile intravitreal implant containing 0.7 mg (700 mcg) dexamethasone in the NOVADUR solid polymer sustained-release drug delivery system which does not contain an antimicrobial preservative.

OZURDEX is preloaded into a single-use, DDS applicator to facilitate injection of the rodshaped implant directly into the vitreous. The NOVADUR system contains two poly D,L-lactide-co-glycolide (PLGA) polymer excipients. Both of these polymer materials have the same PLGA backbone, but the terminal end groups differ between them. One polymer, DL-Lactide and Glycolide (50:50) Copolymer 12000 Ethyl Ester, is ester terminated, and the other DL-Lactide and Glycolide (50:50) Copolymer 12000 Acid is acid terminated. The chemical name for dexamethasone is Pregna-1,4-diene-3,20-dione, 9-fluoro-11,17,21-trihydroxy-16-methyl-, (11β, 16α)-. Its structural formula is:

MW 392.47; molecular formula: C22H29FO5

Dexamethasone occurs as a white to cream-colored crystalline powder having not more than a slight odor, and is practically insoluble in water and very soluble in alcohol.

The PLGA matrix slowly degrades to lactic acid and glycolic acid.

12 CLINICAL PHARMACOLOGY

12.1 Mechanism of Action

Dexamethasone, a corticosteroid, has been shown to suppress inflammation by inhibiting multiple inflammatory cytokines resulting in decreased edema, fibrin deposition, capillary leakage and migration of inflammatory cells.

12.3 Pharmacokinetics

Plasma concentrations were obtained from 21 patients with macular edema due to branch retinal vein occlusion (BRVO) and central retinal vein occlusion (CRVO), and 21 patients with diabetic macular edema (DME) prior to dosing and at 4 to 5 additional post-dose timepoints on Days 1, 7, 21, 30, 45, 60, and 90 following the administration of the first intravitreal implant containing 0.7 mg dexamethasone. In RVO and DME patients, the majority of plasma dexamethasone concentrations were below the lower limit of quantitation (LLOQ = 50 pg/mL). Plasma dexamethasone concentrations from 12% of samples were above the LLOQ, ranging from 52 pg/mL to 102 pg/mL. Plasma dexamethasone concentration did not appear to be related to age, body weight, or sex of patients.

In an in vitro metabolism study, following the incubation of [^14C]-dexamethasone with human cornea, iris-ciliary body, choroid, retina, vitreous humor, and sclera tissues for 18 hours, no metabolites were observed.

13 NONCLINICAL TOXICOLOGY

13.1 Carcinogenesis, Mutagenesis, Impairment of Fertility

Animal studies have not been conducted to determine whether OZURDEX (dexamethasone intravitreal implant) has the potential for carcinogenesis or mutagenesis. Fertility studies have not been conducted in animals.

14 CLINICAL STUDIES

Retinal Vein Occlusion

The efficacy of OZURDEX for the treatment of macular edema following branch retinal vein occlusion (BRVO) or central retinal vein occlusion (CRVO) was assessed in two, multicenter, double-masked, randomized, parallel studies.

Following a single injection, OZURDEX demonstrated the following clinical results for the percent of patients with ≥ 15 letters of improvement from baseline in best-corrected visual acuity (BCVA):

Table 4: Number (Percent) of Patients with ≥ 15 Letters Improvement from Baseline in BCVA
Study Day | Study 1 |  |  | Study 2
 | OZURDEX N=201 | Sham N=202 | p-value* | OZURDEX N=226 | Sham N=224 | p-value*
Day 30 | 40 (20%) | 15 (7%) | < 0.01 | 51 (23%) | 17 (8%) | < 0.01
Day 60 | 58 (29%) | 21 (10%) | < 0.01 | 67 (30%) | 27 (12%) | < 0.01
Day 90 | 45 (22%) | 25 (12%) | < 0.01 | 48 (21%) | 31 (14%) | 0.039
Day 180 | 39 (19%) | 37 (18%) | 0.780 | 53 (24%) | 38 (17%) | 0.087

*P-values were based on the Pearson’s chi-square test.

In each individual study and in a pooled analysis, time to achieve ≥ 15 letters (3-line) improvement in BCVA cumulative response rate curves were significantly faster with OZURDEX compared to sham (p < 0.01), with OZURDEX treated patients achieving a 3-line improvement in BCVA earlier than sham-treated patients.

The onset of a ≥ 15 letter (3-line) improvement in BCVA with OZURDEX occurs within the first two months after implantation in approximately 20-30% of subjects. The duration of effect persists approximately one to three months after onset of this effect.

Posterior Segment Uveitis

The efficacy of OZURDEX was assessed in a single, multicenter, masked, randomized study of 153 patients with non-infectious uveitis affecting the posterior segment of the eye.

After a single injection, the percent of patients reaching a vitreous haze score of 0 (where a score of 0 represents no inflammation) was statistically significantly greater for patients receiving OZURDEX versus sham at week 8 (primary time point) (47% versus 12%). The percent of patients achieving a 3-line improvement from baseline BCVA was 43% for patients receiving OZURDEX versus 7% for sham at week 8.

Diabetic Macular Edema

The efficacy of OZURDEX for the treatment of diabetic macular edema was assessed in two, multicenter, masked, randomized, sham-controlled studies. Subjects were to be evaluated for retreatment eligibility every three months starting from Month 6 but could only receive successive treatments at least 6 months apart. Retreatment was based on physician’s discretion after examination including Optical Coherence Tomography. Patients in the OZURDEX arm received an average of 4 treatments during the 36 months.

The primary endpoint was the proportion of patients with 15 or more letters improvement in BCVA from baseline at Month 39 or final visit for subjects who exited the study at or prior to Month 36. The Month 39 extension was included to accommodate the evaluation of safety and efficacy outcomes for subjects who received re-treatment at Month 36. Only fourteen percent of the study patients completed the Month 39 visit (16.8% from OZURDEX and 12.2% from Sham).

Table 5: Visual Acuity outcomes at Month 39 (All randomized subjects with LOCFc)
Study | Outcomes | OZURDEX | Sham | Estimated Difference (95% CI)
1a | Mean (SD) Baseline BCVA (Letters) | 56 (10) | 57 (9)
 | Median (range) Baseline BCVA (Letters) | 59 (34-95) | 58 (34-74)
 | Gain of ≥15 letters in BCVA (n(%)) | 34 (21%) | 19 (12%) | 9.3% (1.4%, 17.3%)
 | Loss of ≥15 letters in BCVA (n(%)) | 15 (9%) | 17 (10%) | -1.1% (-7.5%, 5.3%)
 | Mean change in BCVA (SD) | 4.1 (13.9) | 0.9 (11.9) | 3.2 (0.4, 5.9)
2b | Mean (SD) Baseline BCVA (Letters) | 55 (10) | 56 (9)
 | Median (range) Baseline BCVA (Letters) | 58 (34-72) | 58 (36-82)
 | Gain of ≥15 letters in BCVA (n(%)) | 30 (18%) | 16 (10%) | 8.4% (0.9%, 15.8%)
 | Loss of ≥15 letters in BCVA (n(%)) | 30 (18%) | 18 (11%) | 7.1% (-0.5%, 14.7%)
 | Mean change in BCVA (SD) | 0.4 (17.5) | 0.8 (13.6) | -0.7 (-4.1, 2.6)

aStudy 1: OZURDEX, N=163; Sham, N=165

bStudy 2: OZURDEX, N=165; Sham, N=163

c14% (16.8% from OZURDEX and 12.2% from Sham) of patients had BCVA outcome at Month 39, for the remaining patients, the data at Month 36 or earlier was carried forward.

Visual acuity outcomes by lens status (Phakic or Pseudophakic) at different visits are presented in Figure 2 and Figure 3. The occurrence of cataracts impacted visual acuity during the study. The visual acuity improvement from baseline increases during a treatment cycle, peaks at approximately 3 Months posttreatment and diminishes thereafter. Patients who were pseudophakic at baseline achieved greater mean BCVA change from baseline at the final study visit.

Figure 2: Proportion of Subjects with ≥ 15 Letters Improvement from Baseline BCVA in the Study Eye

Figure 3: Mean BCVA Change from Baseline

The best corrected visual acuity outcomes for the Pseudophakic and Phakic subgroups from Studies 1 and 2 at Month 39 are presented in Table 6.

Table 6: Visual Acuity outcomes at Month 39 (Subgroup for pooled data with LOCFc)
Subgroup (Pooled) | Outcomes | OZURDEX | Sham | Estimated Difference (95% CI)
aPseudophakic | Gain of ≥15 letters in BCVA (n(%)) | 16 (20%) | 11 (11%) | 8.4% (-2.2%, 19.0%)
 | Loss of ≥15 letters in BCVA (n(%)) | 4 (5%) | 7 (7%) | -2.2% (-9.1%, 4.7%)
 | Mean change in BCVA (SD) | 5.8 (11.6) | 1.4 (12.3) | 4.2 (0.8, 7.6)
bPhakic | Gain of ≥15 letters in BCVA (n(%)) | 48 (20%) | 24 (11%) | 9.0% (2.7%, 15.4%)
 | Loss of ≥15 letters in BCVA (n(%)) | 41 (17%) | 28 (12%) | 4.4% (-1.9%, 10.7%)
 | Mean change in BCVA (SD) | 1.0 (16.9) | 0.6 (12.9) | 0.3 (-2.4, 3.0)

a Pseudophakic: OZURDEX, N=82; Sham, N=99

b Phakic: OZURDEX, N=246; Sham, N=229

c14% (16.8% from OZURDEX and 12.2% from Sham) of patients had BCVA outcome at Month 39, for the remaining patients the data at Month 36 or earlier was used in the analysis.

16 HOW SUPPLIED/STORAGE AND HANDLING

OZURDEX (dexamethasone intravitreal implant) 0.7 mg is supplied in a foil pouch with 1 single-use plastic applicator, NDC 0023-3348-07.

Storage: Store at 15oC to 30oC (59oF to 86oF).

17 PATIENT COUNSELING INFORMATION

Steroid-related Effects

Advise patients that a cataract may occur after repeated treatment with OZURDEX. If this occurs, advise patients that their vision will decrease, and they will need an operation to remove the cataract and restore their vision.

Advise patients that they may develop increased intraocular pressure with OZURDEX treatment, and the increased IOP will need to be managed with eye drops, and, rarely, with surgery.

Intravitreal Injection-related Effects

Advise patients that in the days following intravitreal injection of OZURDEX, patients are at risk for potential complications including in particular, but not limited to, the development of endophthalmitis or elevated intraocular pressure.

When to Seek Physician Advice

Advise patients that if the eye becomes red, sensitive to light, painful, or develops a change in vision, they should seek immediate care from an ophthalmologist.

Driving and Using Machines

Inform patients that they may experience temporary visual blurring after receiving an intravitreal injection. Advise patients not to drive or use machines until this has been resolved.

Distributed by:

AbbVie Inc.
North Chicago, IL 60064

© 2026 AbbVie. All rights reserved.

OZURDEX and its design are trademarks of Allergan, Inc., an AbbVie company.

20095589

PRINCIPAL DISPLAY PANEL

NDC 0023-3348-07
Ozurdex®
(dexamethasone
intravitreal implant) 0.7 mg
For Intravitreal Injection

Rx only

Contents includes:

One Sterile, Single-Use Applicator

Refer to accompanying prescribing information for additional information

abbvie